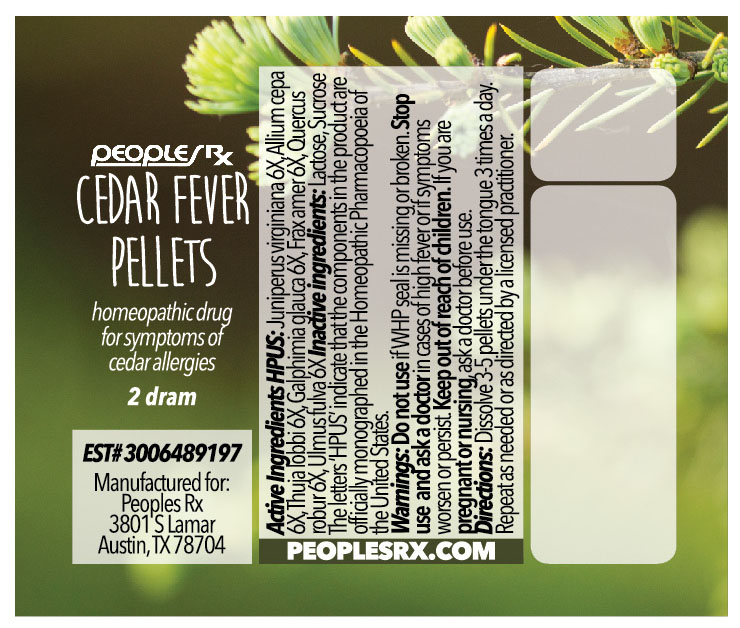 DRUG LABEL: Cedar Fever
NDC: 69406-001 | Form: PELLET
Manufacturer: People's Pharmacy, Inc
Category: homeopathic | Type: HUMAN PRESCRIPTION DRUG LABEL
Date: 20160113

ACTIVE INGREDIENTS: ONION 6 [hp_X]/1 1; FRAXINUS AMERICANA BARK 6 [hp_X]/1 1; GALPHIMIA GLAUCA FLOWERING TOP 6 [hp_X]/1 1; JUNIPERUS VIRGINIANA TWIG 6 [hp_X]/1 1; QUERCUS ROBUR TWIG BARK 6 [hp_X]/1 1; THUJA PLICATA LEAF 6 [hp_X]/1 1; ULMUS RUBRA BARK 6 [hp_X]/1 1
INACTIVE INGREDIENTS: SUCROSE; LACTOSE

DRUG FACTS

ACTIVE INGREDIENTS

JUNIPERUS VIRGINIANA 6X

ALLIUM CEPA 6X

THUJA LOBBI 6X

GALPHIMIA GLAUCA 6X

FRAX AMER 6X

QUERCUS ROBUR 6X

ULMUS FULVA 6X

USES

To relieve the symptoms of cedar allergies.

Keep out of reach of children. If you are pregnant or nursing, ask a doctor before use.

INDICATIONS

JUNIPERUS VIRGINIANA Allergies

ALLIUM CEPA Head cold

THUJA LOBBI Dry, hacking cough

GALPHIMIA GLAUCA Sneezing

FRAX AMER Fever sores on lips

QUERCUS ROBUR Diarrhea

ULMUS FULVA Constipation

WARNINGS

Do not use if WHP seal is missing or broken. Stop use and ask a doctor in cases of high fever or if symptoms persist.

DIRECTIONS

Dissolve 3-5 pellets under the tongue 3 times a day. Repeat as needed or as directed by a licensed practitioner.

INACTIVE INGREDIENTS

Lactose, Sucrose

PRINCIPAL DISPLAY PANEL

Label for 2 dram vial Of Cedar Fever Pellets